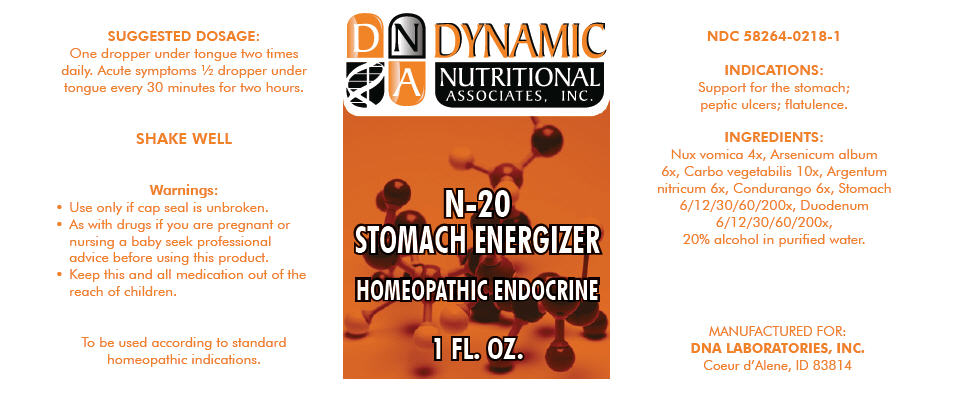 DRUG LABEL: N-20
NDC: 58264-0218 | Form: SOLUTION
Manufacturer: DNA Labs, Inc.
Category: homeopathic | Type: HUMAN OTC DRUG LABEL
Date: 20250109

ACTIVE INGREDIENTS: STRYCHNOS NUX-VOMICA SEED 4 [hp_X]/1 mL; ARSENIC TRIOXIDE 6 [hp_X]/1 mL; ACTIVATED CHARCOAL 10 [hp_X]/1 mL; SILVER NITRATE 6 [hp_X]/1 mL; MARSDENIA CUNDURANGO WHOLE 6 [hp_X]/1 mL; TRIPE 200 [hp_X]/1 mL; SUS SCROFA DUODENUM 200 [hp_X]/1 mL
INACTIVE INGREDIENTS: ALCOHOL; WATER

N-20

NDC 58264-0218-1

INDICATIONS

PURPOSE

Support for the stomach; peptic ulcers; flatulence.

INGREDIENTS

INACTIVE INGREDIENT

Nux vomica 4x, Arsenicum album 6x, Carbo vegetabilis 10x, Argentum nitricum 6x, Condurango 6x, Stomach 6/12/30/60/200x, Duodenum 6/12/30/60/200x, 20% alcohol in purified water.

SUGGESTED DOSAGE

One dropper under tongue two times daily. Acute symptoms ½ dropper under tongue every 30 minutes for two hours.

STORAGE AND HANDLING

SHAKE WELL

Warnings

- Use only if cap seal is unbroken.

PREGNANCY OR BREAST FEEDING

- As with drugs if you are pregnant or nursing a baby seek professional advice before using this product.

KEEP OUT OF REACH OF CHILDREN

- Keep this and all medication out of the reach of children.

To be used according to standard homeopathic indications.

PRINCIPAL DISPLAY PANEL - 1 FL. OZ. Bottle Label

DYNAMIC
NUTRITIONAL
ASSOCIATES, INC.

N-20
STOMACH ENERGIZER

HOMEOPATHIC ENDOCRINE

1 FL. OZ.